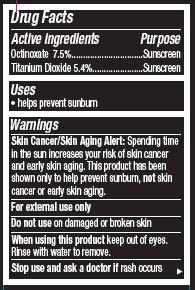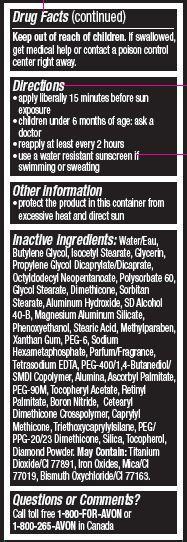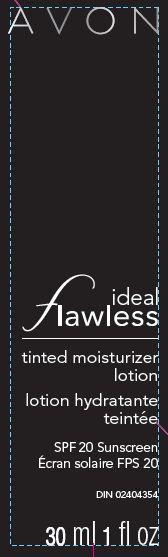 DRUG LABEL: Ideal Flawless
NDC: 10096-0316 | Form: LOTION
Manufacturer: Avon Products, Inc
Category: otc | Type: HUMAN OTC DRUG LABEL
Date: 20131212

ACTIVE INGREDIENTS: OCTINOXATE 75 mg/1 mL; TITANIUM DIOXIDE 54 mg/1 mL

Active ingredient
Octinoxate 7.5%..................
Titanium Dioxide 5.4%......................

Purpose
.................................Sunscreen

.................................Sunscreen

Uses
• helps prevent sunburn

Warnings

Skin Cancer/Skin Aging Alert: Spending time in the sun increases your risk of skin cancer and early skin aging. This product has been
shown only to help prevent sunburn, not skin cancer or early skin aging.

For external use only

Do not use on damaged or broken skin

When using this product keep out of eyes. Rinse with water to remove.

Stop use and ask a doctor if rash occurs

Keep out of reach of children. If swallowed, get medical help or contact a Poison Control Center right away.

Directions
• apply liberally 15 minutes before sun exposure
• children under 6 months of age: ask a doctor
• reapply at least every 2 hours
• use a water resistant sunscreen if swimming or sweating

Other information

• protect the product in this container from excessive heat and direct sun

Inactive Ingredients:
Water/Eau, Butylene Glycol, Isocetyl Stearate, Glycerin, Propylene Glycol Dicaprylate/Dicaprate, Octyldodecyl Neopentanoate, Polysorbate 60, Glycol Stearate, Dimethicone, Sorbitan Stearate, Aluminum Hydroxide, SD Alcohol 40-B, Magnesium Aluminum Silicate, Phenoxyethanol, Stearic Acid, Methylparaben, Xanthan Gum, PEG-6, Sodium Hexametaphosphate, Parfum/Fragrance, Tetrasodium EDTA, PEG-400/1,4-Butanediol/SMDI Copolymer, Alumina, Ascorbyl Palmitate, PEG-90M, Tocopheryl Acetate, Retinyl Palmitate, Boron Nitride, Cetearyl Dimethicone Crosspolymer, Caprylyl Methicone, Triethoxycaprylylsilane, PEG/PPG-20/23 Dimethicone, Silica, Tocopherol, Diamond Powder. May Contain: Titanium Dioxide/CI 77891, Iron Oxides, Mica/CI 77019, Bismuth Oxychloride/CI 77163

Questions or Comments?
Call toll free 1-800-FOR-AVON or 1-800-265-AVON in Canada